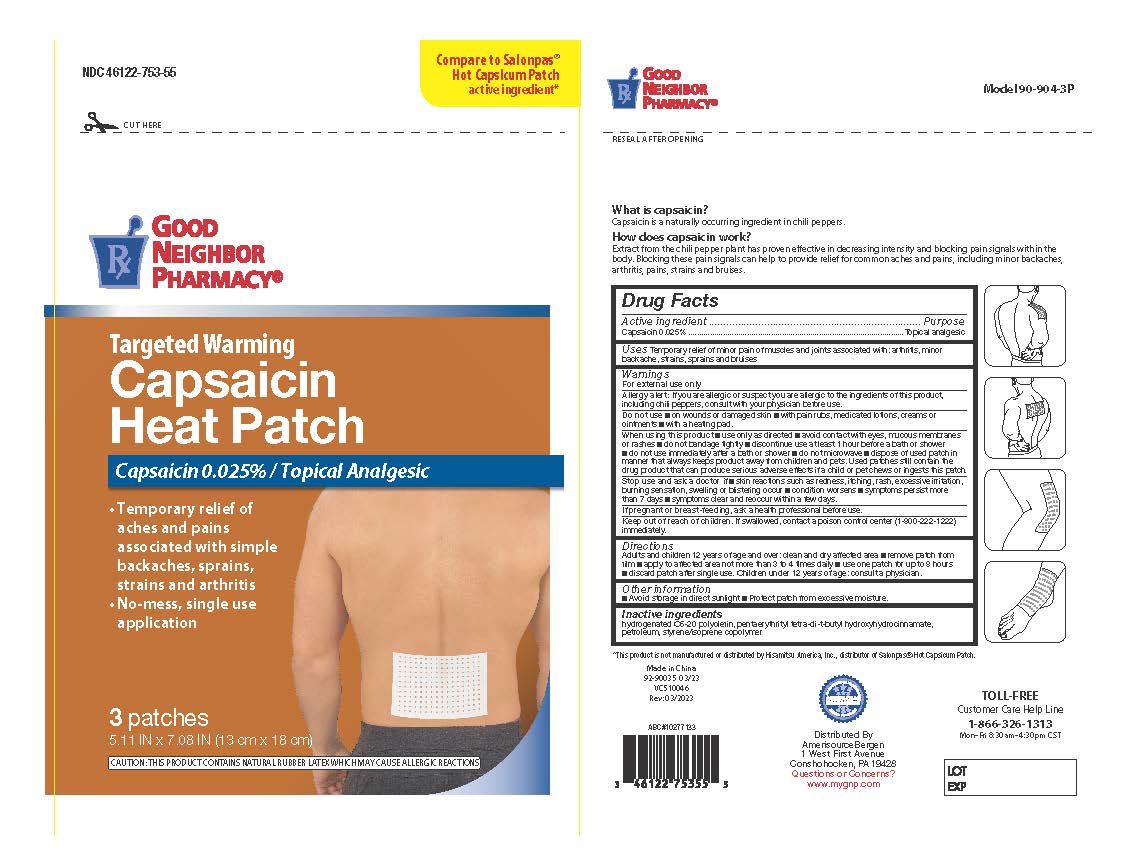 DRUG LABEL: Good Neighbor Capsaicin Heat Patch for Back
NDC: 46122-753 | Form: PATCH
Manufacturer: Amerisource Bergen
Category: otc | Type: HUMAN OTC DRUG LABEL
Date: 20251222

ACTIVE INGREDIENTS: CAPSAICIN 0.025 g/100 g
INACTIVE INGREDIENTS: STYRENE/ISOPRENE/STYRENE BLOCK COPOLYMER; HYDROGENATED C6-20 POLYOLEFIN (100 CST); SILICON DIOXIDE; PENTAERYTHRITOL TETRAKIS(3-(3,5-DI-TERT-BUTYL-4-HYDROXYPHENYL)PROPIONATE); LIQUID PETROLEUM

Good Neighbor Capsaicin Heat Patch for Back Lrg 3-Ct

Active ingredient

Capsicum extract 0.025% as Capsaicin

Purpose

Topical analgesic

Uses

For temporary relief of minor aches and pains of muscles and joints associated with:

- minor backache
- arthritis
- strains
- bruises
- sprains

Warnings

For external use only

Do not use

ALLERGY ALERT:

If you are allergic or suspect you are allergic to the ingredients of this product,
including chili peppers, consult with your physician before use.

Do not use

- on wounds or damaged skin
- with a heating pad
- if you are allergic to any ingredients of this product

When using this product

- use only as directed
- avoid contact with the eyes, mucous membranes or rashes
- do not bandage tightly
- discontinue use at least 1 hour before a bath or shower
- do not use immediately after a bath or shower

Stop use and ask a doctor if

- skin reactions such as redness, rash, itching, excessive irritation burning sensation, swelling or blistering occurs ■ condition worsens ■ symptoms persist more
  than 7 days ■ symptoms clear and reoccur within a few days.

If pregnant or breast-feeding,

ask a health professional before use.

Keep out of reach of children.

If swallowed, get medical help or contact a Poison Control Center (1-800-222-1222) immediately.

Directions

Adults and children 12 years of age and over:

- clean and dry affected area
- remove patch from film
- apply to affected area not more than 3 to 4 times daily
- use one patch for up to 8 hours
- discard patch after single use

Children under 12 years of age: consult a physician

Other information

- Avoid storing product in direct sunlight
- Protect product from excessive moisture

Inactive ingredients

hydrogenated C6-20 polyolefin, pentaerythrityl tetra-di-t-butyl hydroxyhydrocinnamate,
petroleum, styrene/isoprene copolymer

Questions or comments?

Toll free 1-866-326-1313